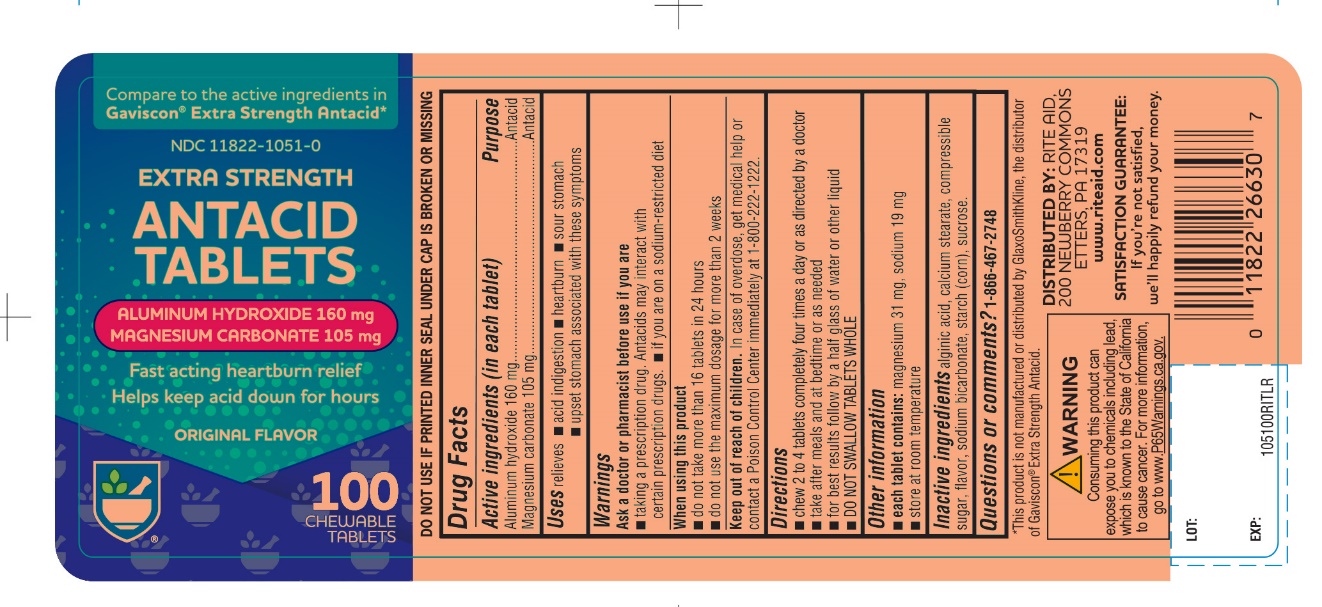 DRUG LABEL: Rite Aid Extra Strength
NDC: 11822-1051 | Form: TABLET, CHEWABLE
Manufacturer: RITE AID CORPORATION
Category: otc | Type: HUMAN OTC DRUG LABEL
Date: 20241030

ACTIVE INGREDIENTS: ALUMINUM HYDROXIDE 160 mg/1 1; MAGNESIUM CARBONATE 105 mg/1 1
INACTIVE INGREDIENTS: ALGINIC ACID; CALCIUM STEARATE; CORN SYRUP; SODIUM BICARBONATE; STARCH, CORN; SUCROSE

Extra Strength 100 Chewable Antacid Tablets

Active ingredients (in each tablet)

Aluminum hydroxide 160 mg

Magnesium carbonate 105 mg

Purpose

Antacid

Antacid

Uses

relieves

- acid indigestion
- heartburn
- sour stomach
- upset stomach associated with these symptoms

Warnings

Ask a doctor or pharmacist before use if you are

- taking a prescription drug. Antacids may interact with certain prescription drugs
- on a sodium-restricted diet

When using this product

- do not take more than 16 tablets in 24 hours
- do not use the maximum dosage for more than 2 weeks

Keep out of reach of children.

In case of overdose, get medical help or contact a Poison Control Center immediately at 1-800-222-1222.

Directions

- chew 2 to 4 tablets four times a day
- take after meals and at bedtime or as needed
- for best results follow by a half glass of water or other liquid
- do not swallow tablets whole

Other information

- each tablet contains: sodium 19 mg, magnesium 31 mg
- Do not use if printed seal under cap is torn or missing
- Store at up to 25°C (77°F) in a dry place.

Inactive ingredients

alginic acid, calcium stearate, compressible sugar, flavor, sodium bicarbonate, starch (corn), sucrose.

Questions or comments?

1-866-467-2748

Principal Display Panel

RITE AID PHARMACY®

NDC 11822-1051-0

Compare to the active ingredients Gaviscon® Extra Strength.

Extra Strength

Antacid

Aluminum Hydroxide, 160 mg

Magnesium Carbonate, 105 mg

fast-acting
heartburn relief
helps keep acid down for hours

100 CHEWABLE TABLETS

DISTRIBUTED BY:

RITE AID, 30 HUNTER LANE

CAMP HILL, PA 17011

MADE IN USA

IF YOU’RE NOT SATISFIED, WE’ALL HAPPILY REFUND YOUR MONEY.

*This product is not manufactured or distributed by GlaxoSmithKline, the distributor of Gaviscon® Extra Strength Antacid.